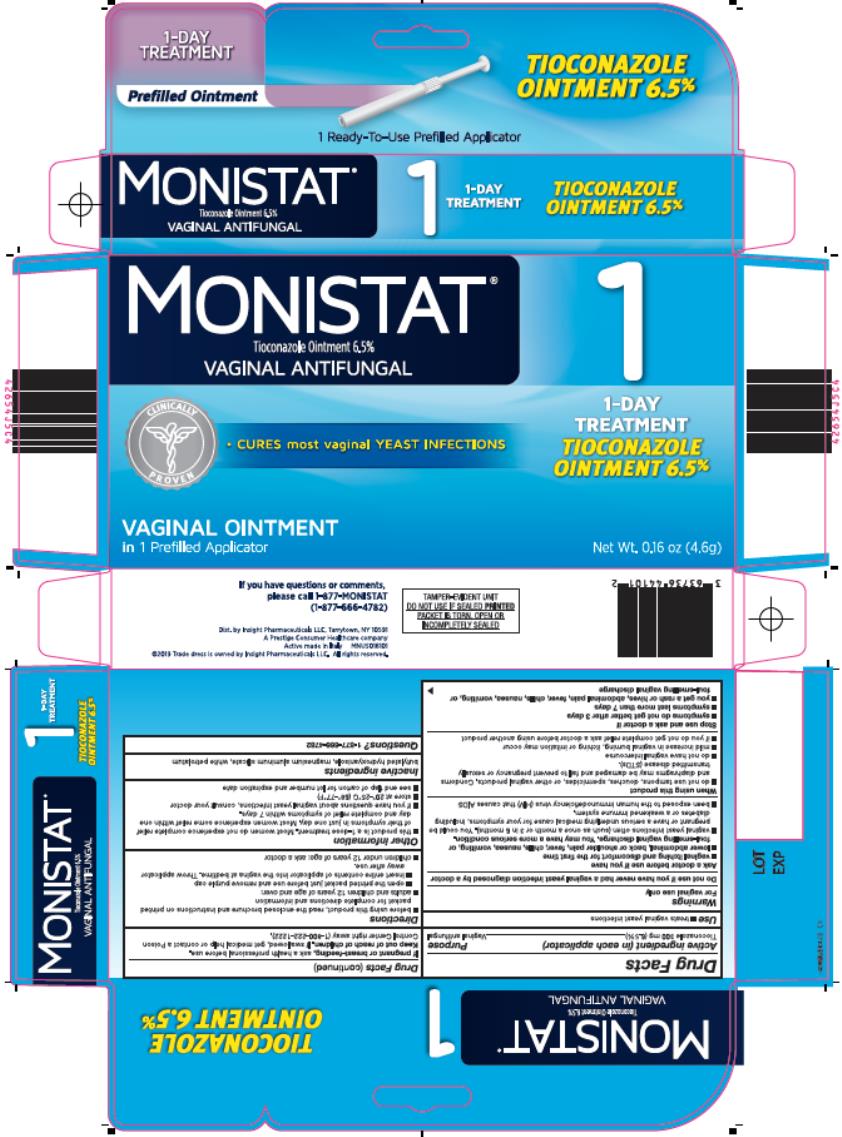 DRUG LABEL: MONISTAT TIOCONAZOLE 1
NDC: 63736-413 | Form: OINTMENT
Manufacturer: Insight Pharmaceuticals LLC
Category: otc | Type: HUMAN OTC DRUG LABEL
Date: 20190319

ACTIVE INGREDIENTS: TIOCONAZOLE 6.5 g/100 g
INACTIVE INGREDIENTS: BUTYLATED HYDROXYANISOLE; MAGNESIUM ALUMINUM SILICATE; PETROLATUM

Monistat Tioconazole Ointment

Drug Facts

Active ingredient (in each applicator)

Tioconazole 300 mg (6.5%)

Purpose

Vaginal antifungal

Uses

- treats vaginal yeast infections

Warnings

For vaginal use only

Do not use

if you have never had a vaginal yeast infection diagnosed by a doctor.

Ask a doctor before use if you have

- vaginal itching and discomfort for the first time
- lower abdominal, back or shoulder pain, fever, chills, nausea, vomiting, or foul-smelling vaginal discharge. You may have a more serious condition.
- vaginal yeast infections often (such as once a month or 3 in 6 months). You could be pregnant or have a serious underlying medical cause for your symptoms, including diabetes or a weakened immune system.
- been exposed to the human immunodeficiency virus (HIV) that causes AIDS

When using this product

- do not use tampons, douches, spermicides or other vaginal products. Condoms and diaphragms may be damaged and fail to prevent pregnancy or sexually transmitted diseases (STDs).
- do not have vaginal intercourse
- mild increase in vaginal burning, itching or irritation may occur
- if you do not get complete relief ask a doctor before using another product

Stop use and ask a doctor if:

- symptoms do not get better in 3 days
- symptoms last more than 7 days
- you get a rash or hives, abdominal pain, fever, chills, nausea, vomiting , or foul-smelling vaginal discharge.

If pregnant or breast-feeding

ask a health professional before use

Keep out of reach of children.

If swallowed, get medical help or contact a Poison Control Center right away (1-800-222-1222).

Directions

- before using this product read the enclosed brochure and instructions on foil packet for complete directions and information
- adults and children 12 years of age and over:
  ○ open the foil packet just before use and remove purple cap
  ○ insert entire content of applicator into the vagina at bedtime. Throw applicator away after use.
- children under 12 years of age: ask a doctor.

Other information

- this product is a 1-dose treatment. Most women do not get complete relief of their symptoms in just one day. Most women get some improvement in one day and complete relief of symptoms within 7 days.
- if you have questions about vaginal yeast infections, consult your doctor
- store at 20°-25°C (68°-77°F)
- see end flap of carton for lot number and expiration date

Inactive ingredients

butylated hydroxyanisole, magnesium aluminum silicate, white petrolatum

Questions?

1-877-666-4782

PRINCIPAL DISPLAY PANEL

MONISTAT®

Tioconazole Ointment 6.5%

VAGINAL ANTIFUNGAL

Net Wt. 0.16 OZ (4.6 g) PREFILLED APPLICATOR